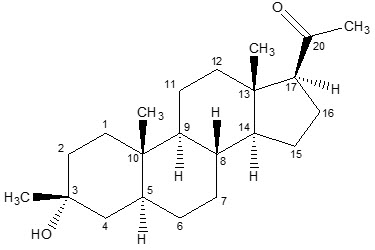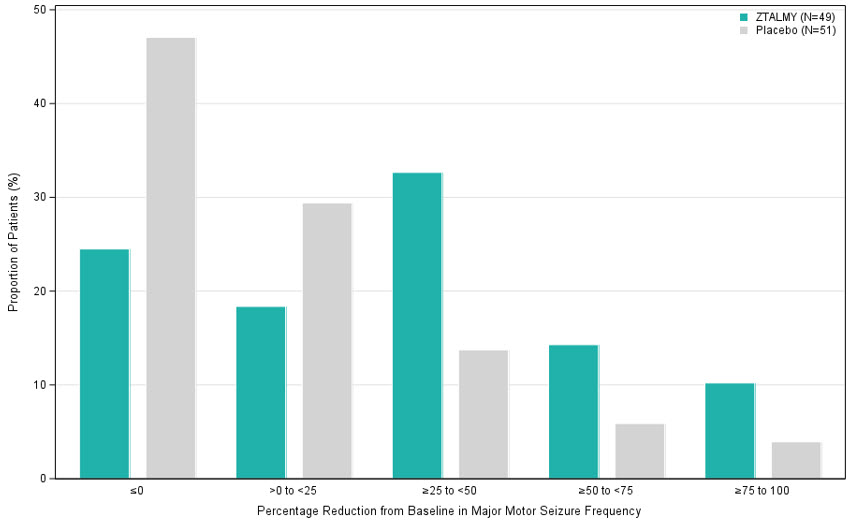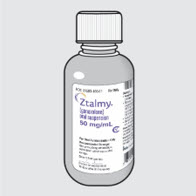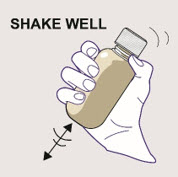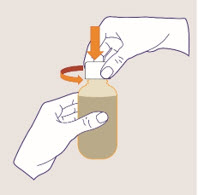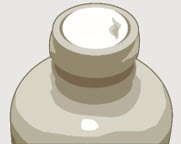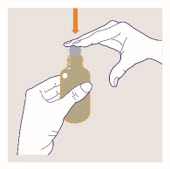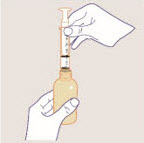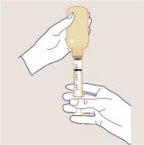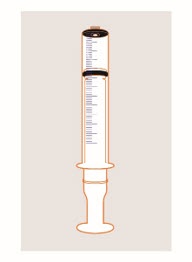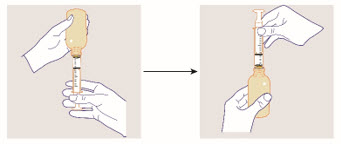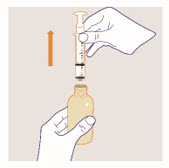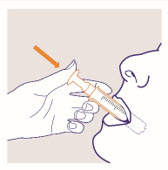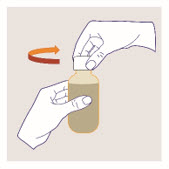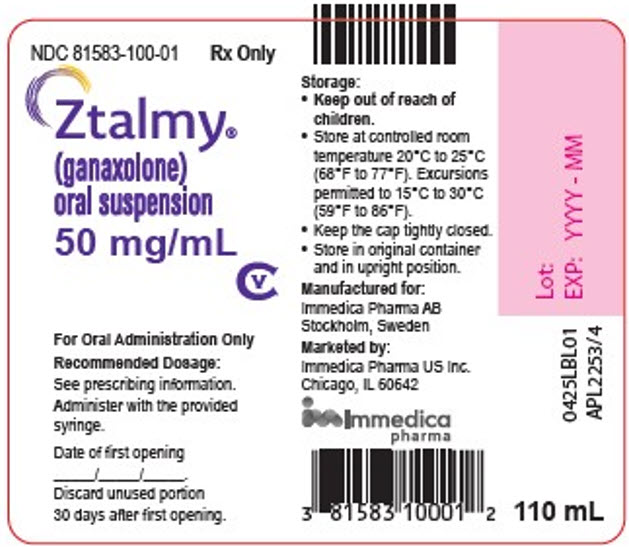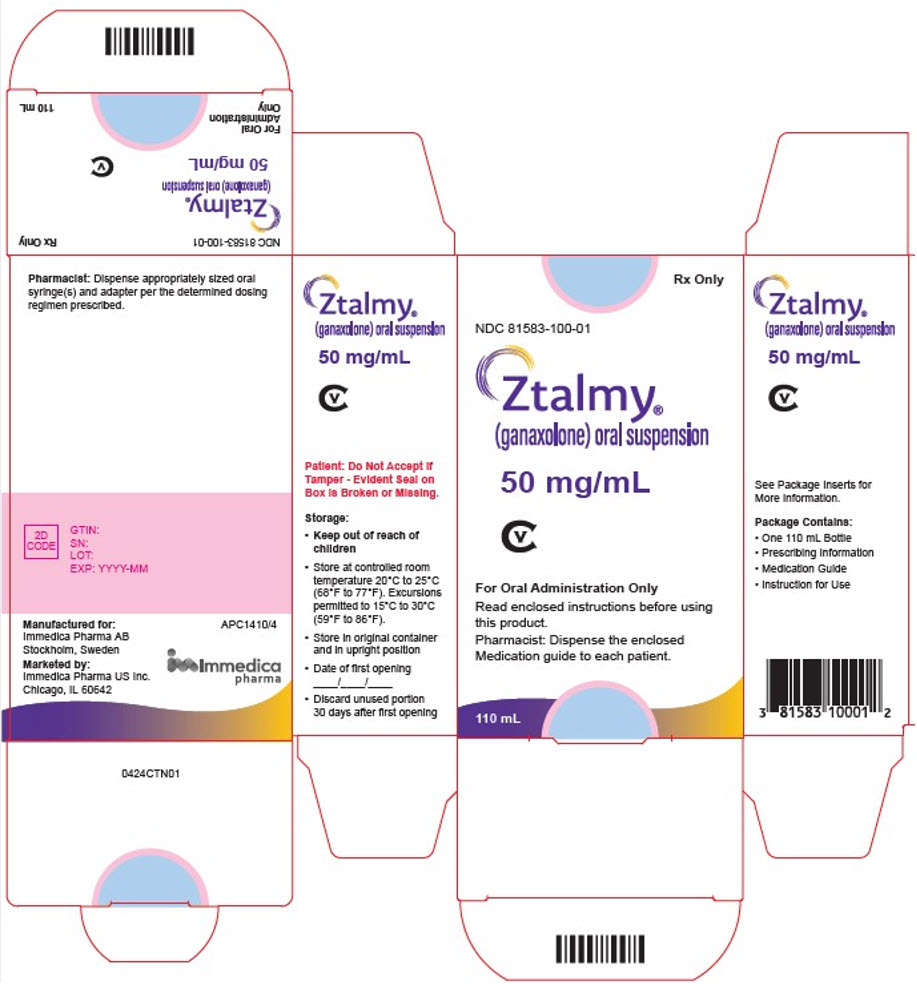 DRUG LABEL: ZTALMY
NDC: 81583-100 | Form: SUSPENSION
Manufacturer: Immedica Pharma US Inc
Category: prescription | Type: HUMAN PRESCRIPTION DRUG LABEL
Date: 20251128
DEA Schedule: CV

ACTIVE INGREDIENTS: GANAXOLONE 50 mg/1 mL
INACTIVE INGREDIENTS: ANHYDROUS CITRIC ACID; HYPROMELLOSE, UNSPECIFIED; METHYLPARABEN; POLYVINYL ALCOHOL, UNSPECIFIED; PROPYLPARABEN; WATER; SODIUM BENZOATE; SODIUM CITRATE, UNSPECIFIED FORM; SODIUM LAURYL SULFATE; SUCRALOSE

HIGHLIGHTS OF PRESCRIBING INFORMATION

These highlights do not include all the information needed to use ZTALMY®safely and effectively. See full prescribing information for ZTALMY.
ZTALMY®(ganaxolone) oral suspension, CV
Initial U.S. Approval: 2022

RECENT MAJOR CHANGES

Dosage and Administration (2.1, 2.3) | 10/2025

1 INDICATIONS AND USAGE

ZTALMY is a neuroactive steroid gamma-aminobutyric acid (GABA) A receptor positive modulator indicated for the treatment of seizures associated with cyclin-dependent kinase-like 5 (CDKL5) deficiency disorder (CDD) in patients 2 years of age and older. (1)

2 DOSAGE AND ADMINISTRATION

- Administer ZTALMY orally three times daily with food. (2.1)
- Titrate ZTALMY gradually according to the recommended schedules. See full prescribing information. (2.1)
- Dosage for patients weighing 28 kg or less (2.1):
  - the starting dosage is 2 mg/kg three times daily (6 mg/kg/day)
  - the maximum dosage is 21 mg/kg three times daily (63 mg/kg/day).
- Dosage for patients weighing over 28 kg (2.1):
  - the starting dosage is 50 mg three times daily (150 mg daily)
  - the maximum dosage is 600 mg three times daily (1800 mg daily).
- Patients with severe hepatic impairment: see full prescribing information for dosage recommendation. (2.3)

3 DOSAGE FORMS AND STRENGTHS

Oral suspension 50 mg/mL (3)

4 CONTRAINDICATIONS

None. (4)

5 WARNINGS AND PRECAUTIONS

- Somnolence and Sedation: Monitor for somnolence and sedation and advise patients not to drive or operate machinery until they have gained sufficient experience with ZTALMY. Concomitant use with other CNS depressants or alcohol could potentiate adverse effects. (5.1)
- Suicidal Behavior and Ideation: Monitor patients for suicidal behavior and thoughts. (5.2)
- Withdrawal of Antiepileptic Drugs: ZTALMY should be withdrawn gradually to minimize the risk of increased seizure frequency and status epilepticus. (5.3)

6 ADVERSE REACTIONS

Most common adverse reactions (incidence of at least 5% for ZTALMY and at least twice the rate of placebo) are somnolence, pyrexia, salivary hypersecretion, and seasonal allergy. (6.1)

To report SUSPECTED ADVERSE REACTIONS, contact Immedica at 1-844-627-4687 or FDA at 1-800-FDA-1088 or www.fda.gov/medwatch.

7 DRUG INTERACTIONS

- UGT inhibitors may increase ganaxolone exposures; consider reduction of a stable ZTALMY dosage when initiating a UGT inhibitor. (7.1)
- Cytochrome P450 inducers will decrease ganaxolone exposure. It is recommended to avoid concomitant use with strong or moderate CYP3A4 inducers; if unavoidable, consider a dosage increase of ZTALMY, but do not exceed the maximum recommended dosage. (7.2)

8 USE IN SPECIFIC POPULATIONS

- Pregnancy: Based on animal data, may cause fetal harm. (8.1)

FULL PRESCRIBING INFORMATION

1 INDICATIONS AND USAGE

ZTALMY is indicated for the treatment of seizures associated with cyclin-dependent kinase-like 5 (CDKL5) deficiency disorder (CDD) in patients 2 years of age and older.

2 DOSAGE AND ADMINISTRATION

2.1 Dosage Information

ZTALMY is administered by mouth three times daily and must be taken with food [see Clinical Pharmacology (12.3)] .

The recommended titration schedule and maintenance dosage are based on body weight for patients weighing 28 kg or less. Dosage recommendations for patients weighing 28 kg or less are included in Table 1, and dosage recommendations for patients weighing more than 28 kg are included in Table 2. Dosage should be increased based on tolerability no more frequently than every 7 days. Titration increments should not exceed those shown in Table 1 and Table 2.

Table 1 ZTALMY Recommended Titration Schedule for Patients Weighing 28 kg or Less
Dosage | Total Daily Dose | Day
2 mg/kg three times daily | 6 mg/kg/day | 1 to 7
4 mg/kg three times daily | 12 mg/kg/day | 8 to 14
8 mg/kg three times daily | 24 mg/kg/day | 15 to 21
14 mg/kg three times daily | 42 mg/kg/day | 22 to 28
21 mg/kg three times daily | 63 mg/kg/day | 29 and thereafter

Table 2 ZTALMY Recommended Titration Schedule for Patients Weighing More Than 28 kg
Dosage | Total Daily Dose | Day
50 mg three times daily | 150 mg | 1 to 7
100 mg three times daily | 300 mg | 8 to 14
200 mg three times daily | 600 mg | 15 to 21
400 mg three times daily | 1,200 mg | 22 to 28
600 mg three times daily | 1,800 mg | 29 and thereafter

2.2 Administration Instructions

See the Instructions for Usefor complete instructions on how to properly prepare and administer ZTALMY.

Shake the bottle thoroughly for at least 1 minute and then wait for 1 minute before measuring and administering each dose.

Measure and administer the prescribed dose using the oral syringe(s) provided by your pharmacist. A household teaspoon or tablespoon is not an adequate measuring device and should not be used.

ZTALMY must be administered with food [see Clinical Pharmacology (12.3)] .

Discard any unused ZTALMY oral suspension after 30 days of first opening the bottle [see How Supplied/Storage and Handling (16.2)] .

2.3 Dosage in Patients with Severe Hepatic Impairment

ZTALMY is administered by mouth three times daily and must be taken with food [see Clinical Pharmacology (12.3)] .

The recommended titration schedule and maintenance dosage are based on body weight for patients weighing 28 kg or less. Dosage recommendations for patients with severe hepatic impairment and weighing 28 kg or less are included in Table 3, and dosage recommendations for patients with severe hepatic impairment (Child-Pugh class C) weighing more than 28 kg are included in Table 4. Dosage should be increased based on tolerability no more frequently than every 7 days. Titration increments should not exceed those shown in Table 3 and Table 4.

No dosage adjustment is necessary in patients with mild (Child-Pugh class A) or moderate (Child-Pugh class B) hepatic impairment.

Table 3 ZTALMY Recommended Titration Schedule for Patients with Severe Hepatic Impairment and Weighing 28 kg or Less
Dosage | Total Daily Dose [Approximate daily dose.] | Days
0.66 mg/kg three times daily | 2 mg/kg/day | 1 to 7
1.33 mg/kg three times daily | 4 mg/kg/day | 8 to 14
2.66 mg/kg three times daily | 8 mg/kg/day | 15 to 21
4.66 mg/kg three times daily | 14 mg/kg/day | 22 to 28
7 mg/kg three times daily | 21 mg/kg/day | 29 and thereafter

Table 4 ZTALMY Recommended Titration Schedule for Patients with Severe Hepatic Impairment and Weighing More Than 28 kg
Dosage | Total Daily Dose [Approximate daily dose.] | Days
17 mg three times daily | 50 mg | 1 to 7
33 mg three times daily | 100 mg | 8 to 14
67 mg three times daily | 200 mg | 15 to 21
133 mg three times daily | 400 mg | 22 to 28
200 mg three times daily | 600 mg | 29 and thereafter

2.4 Discontinuation of ZTALMY

Decrease the dose of ZTALMY gradually when discontinuing treatment. As with all antiepileptic drugs, abrupt discontinuation should be avoided, when possible, to minimize the risk of increased seizure frequency and status epilepticus [see Warnings and Precautions (5.3)] .

3 DOSAGE FORMS AND STRENGTHS

Oral suspension: 50 mg/mL ganaxolone. Each bottle contains 110 mL of white to off-white cherry flavored suspension.

4 CONTRAINDICATIONS

None.

5 WARNINGS AND PRECAUTIONS

5.1 Somnolence and Sedation

ZTALMY can cause somnolence and sedation. In Study 1 [see Clinical Studies (14)] , the incidence of somnolence and sedation was 44% in patients treated with ZTALMY, compared with 24% in patients receiving placebo. Somnolence and sedation appeared early during treatment and were generally dose-related [see Adverse Reactions (6.1)] .

Other central nervous system (CNS) depressants, including opioids, antidepressants, and alcohol, could potentiate somnolence and sedation in patients receiving ZTALMY [see Clinical Pharmacology (12.3)] . Prescribers should monitor patients for somnolence and sedation, and advise patients not to drive or operate machinery until they have gained sufficient experience on ZTALMY to gauge whether it adversely affects their ability to drive or operate machinery.

5.2 Suicidal Behavior and Ideation

Antiepileptic drugs (AEDs), including ZTALMY, increase the risk of suicidal thoughts or behavior in patients taking these drugs for any indication. Patients treated with an AED for any indication should be monitored for the emergence or worsening of depression, suicidal thoughts or behavior, or any unusual changes in mood or behavior.

Pooled analyses of 199 placebo-controlled clinical trials (mono- and adjunctive therapy) of 11 different AEDs, that did not include ZTALMY, showed that patients randomized to one of the AEDs had approximately twice the risk (adjusted Relative Risk 1.8, 95% CI:1.2, 2.7) of suicidal thinking or behavior compared to patients randomized to placebo. In these trials, which had a median treatment duration of 12 weeks, the estimated incidence rate of suicidal behavior or ideation among 27,863 AED-treated patients was 0.43%, compared to 0.24% among 16,029 placebo-treated patients, representing an increase of approximately one case of suicidal thinking or behavior for every 530 patients treated. There were 4 suicides in drug-treated patients in the trials and none in placebo-treated patients, but the number is too small to allow any conclusion about drug effect on suicide.

The increased risk of suicidal thoughts or behavior with AEDs was observed as early as 1 week after starting drug treatment with AEDs and persisted for the duration of treatment assessed. Because most trials included in the analysis did not extend beyond 24 weeks, the risk of suicidal thoughts or behavior beyond 24 weeks could not be assessed.

The risk of suicidal thoughts or behavior was generally consistent among drugs in the data analyzed. The finding of increased risk with AEDs of varying mechanisms of action and across a range of indications suggests that the risk applies to all AEDs used for any indication. The risk did not vary substantially by age (5–100 years) in the clinical trials analyzed. Table 5 shows absolute and relative risk by indication for all evaluated AEDs.

Table 5 Risk of Suicidal Thoughts or Behaviors by Indication for Antiepileptic Drugs in the Pooled Analysis
Indication | Placebo Patients with Events per 1000 Patients | Drug Patients with Events per 1000 Patients | Relative Risk: Incidence of Events in Drug Patients/ Incidence in Placebo Patients | Risk Difference: Additional Drug Patients with Events per 1000 Patients
Epilepsy | 1.0 | 3.4 | 3.5 | 2.4
Psychiatric | 5.7 | 8.5 | 1.5 | 2.9
Other | 1.0 | 1.8 | 1.9 | 0.9
Total | 2.4 | 4.3 | 1.8 | 1.9

The relative risk for suicidal thoughts or behavior was higher in clinical trials in patients with epilepsy than in clinical trials in patients with psychiatric or other conditions, but the absolute risk differences were similar for the epilepsy and psychiatric indications.

Anyone considering prescribing ZTALMY, or any other AED must balance the risk of suicidal thoughts or behaviors with the risk of untreated illness. Epilepsy and many other illnesses for which AEDs are prescribed are themselves associated with morbidity and mortality and an increased risk of suicidal thoughts and behavior. Should suicidal thoughts and behavior emerge during treatment, consider whether the emergence of these symptoms in any given patient may be related to the illness being treated.

5.3 Withdrawal of Antiepileptic Drugs

As with most AEDs, ZTALMY should be withdrawn gradually because of the risk of increased seizure frequency and status epilepticus [see Dosage and Administration (2.4)] . If withdrawal is needed because of a serious adverse event, rapid discontinuation can be considered.

6 ADVERSE REACTIONS

The following important adverse reactions are described elsewhere in the labeling:

- Somnolence and Sedation [see Warnings and Precautions (5.1)]
- Suicidal Behavior and Ideation [see Warnings and Precautions (5.2)]
- Withdrawal of Antiepileptic Drugs [see Warnings and Precautions (5.3)]

6.1 Clinical Trials Experience

Because clinical trials are conducted under widely varying conditions, adverse reaction rates observed in the clinical trials of a drug cannot be directly compared to rates in the clinical trials of another drug and may not reflect the rates observed in practice.

In controlled and uncontrolled trials in patients with seizures associated with CDD, 102 patients were treated with ZTALMY, including 83 patients treated for more than 6 months, and 50 patients treated for more than 1 year.

In Study 1, 50 patients received ZTALMY [see Clinical Studies (14)] . The duration of treatment in this trial was up to 17 weeks. Approximately 78% of these patients were female, 92% were White, and the mean age was 6.8 years (range 2 to 19 years). All patients receiving ZTALMY, except 1, were taking other AEDs. Adverse reactions in these patients are presented below.

The most common adverse reactions (an incidence of at least 5% and at least twice the rate of placebo) were somnolence, pyrexia, salivary hypersecretion, and seasonal allergy (Table 6).

The adverse reactions leading to treatment discontinuation in ZTALMY-treated patients were somnolence and seizure (1 patient) and seizure (1 patient).

Twenty-two percent of ZTALMY-treated patients had dosing interrupted or reduced because of any adverse reaction, compared to 16% of placebo-treated patients. The most frequent adverse reactions leading to a dose interruption or reduction in ZTALMY-treated patients were somnolence (10%) and sedation (2%).

Table 6 presents the adverse reactions that occurred in ZTALMY-treated patients with seizures associated with CDD at a rate of at least 3% and at a rate greater than in placebo-treated patients during the double-blind phase.

Table 6 Adverse Reactions that Occurred in ZTALMY-Treated Patients with Seizures Associated with CDD at a Rate of At Least 3% and Greater Than in Placebo (Study 1)
Adverse Reactions | ZTALMY (N=50) | Placebo (N=51)
 | % | %
Somnolence [somnolence includes the terms lethargy and hypersomnia] [adverse reactions that occurred with a 21-day titration; somnolence and sedation are expected to be reduced with the recommended 28-day titration [see Dosage and Administration (2.1, 2.3)]] | 38 | 20
Pyrexia | 18 | 8
Upper respiratory tract infection | 10 | 6
Sedation | 6 | 4
Salivary Hypersecretion | 6 | 2
Seasonal allergy | 6 | 0
Bronchitis | 4 | 0
Influenza | 4 | 2
Gait disturbance | 4 | 2
Nasal congestion | 4 | 2

7 DRUG INTERACTIONS

7.1 Effect of UGT Inhibitors on ZTALMY

Concomitant use of ZTALMY and UGT inhibitors (e.g., valproic acid) may increase the exposure of ganaxolone, which may increase the risk of ZTALMY associated adverse reactions in patients who have titrated to a stable ZTALMY dosage. Consider a reduction of ZTALMY maintenance dosage when initiating a UGT inhibitor [see Clinical Pharmacology (12.3)].

7.2 Effect of Strong or Moderate Cytochrome P450 Inducers on ZTALMY

Coadministration of ZTALMY with CYP450 inducers, such as strong or moderate CYP3A4 inducers, will decrease ganaxolone exposure, which can lower the efficacy of ZTALMY [see Clinical Pharmacology (12.3)] .

It is recommended to avoid concomitant use of strong or moderate CYP3A4 inducers with ZTALMY. When concomitant use of strong or moderate CYP3A4 inducers is unavoidable, consider an increase in the dosage of ZTALMY; however, do not exceed the maximum daily dosage of ZTALMY [see Dosage and Administration (2.1)] .

In patients on a stable ZTALMY dosage who are initiating or increasing the dosages of enzyme-inducing antiepileptic drugs (e.g., carbamazepine, phenytoin, phenobarbital, and primidone), the ZTALMY dosage may need to be increased; however, do not exceed the maximum daily dosage of ZTALMY [see Dosage and Administration (2.1)] .

7.3 Concomitant Use of ZTALMY with CNS Depressants and Alcohol

Concomitant use of ZTALMY with CNS depressants, including alcohol, may increase the risk of somnolence and sedation [see Warnings and Precautions (5.1)] .

8 USE IN SPECIFIC POPULATIONS

8.1 Pregnancy

Pregnancy Exposure Registry

There is a pregnancy exposure registry that monitors pregnancy outcomes in women exposed to antiepileptic drugs (AEDs), such as ZTALMY, during pregnancy. Encourage women who are taking ZTALMY during pregnancy to enroll in the North American Antiepileptic Drug (NAAED) Pregnancy Registry by calling the toll-free number 1-888-233-2334 or visiting http://www.aedpregnancyregistry.org/.

Risk Summary

There are no available data on ZTALMY use in pregnant women to inform a drug-associated risk of adverse developmental outcomes. In animal studies, adverse effects on development were observed in mice (fetal malformations) and rats (neurobehavioral and growth impairment) following exposure during organogenesis (mouse) or throughout gestation and lactation (rat) at maternal exposures lower than that in human adults at the maximum recommended human dose (MRHD) of 1800 mg. In addition, neuronal death was observed in rats exposed to ganaxolone during a period of brain development that begins during the third trimester of pregnancy in humans and continues during the first few years after birth.

In the US general population, the estimated background risk of major birth defects and miscarriage in clinically recognized pregnancies is 2% to 4% and 15% to 20%, respectively. The background risks of major birth defects and miscarriage for the indicated populations are unknown.

Clinical Considerations

Disease-associated Maternal and/or Embryofetal Risk

Epilepsy, with or without exposure to antiepileptic drugs, has been associated with several adverse outcomes during pregnancy, including preeclampsia, preterm labor, antepartum and postpartum hemorrhage, placental abruption, poor fetal growth, prematurity, fetal death, and maternal mortality. The risk of maternal or fetal injury may be greatest for patients with untreated or poorly controlled convulsive seizures. Women with epilepsy who become pregnant should not abruptly discontinue antiepileptic drugs, including ZTALMY, due to the risk of status epilepticus or severe seizures, which may be life-threatening [see Warnings and Precautions (5.3)].

Data

Animal Data

In an embryofetal development study in mice, oral administration of ganaxolone (0, 50, 175, or 300 mg/kg/day) throughout the period of organogenesis resulted in increased incidences of fetal malformations (external and/or visceral) at all doses in the absence of maternal toxicity. Maternal plasma drug exposures (AUC) at the low-effect dose (50 mg/kg/day) for embryofetal developmental toxicity in the mouse were approximately 10-fold lower than that in humans at the MRHD.

In a combined embryofetal development and pre- and postnatal development study in rats, ganaxolone (0, 10, 20, or 40 mg/kg/day) was administered orally to females throughout gestation and lactation. There were no effects on embryofetal growth, survival, or morphology; however, adverse effects on offspring growth (delayed reflex development, decreased body weight gain) were observed during the postnatal period (prior to and after weaning) at the high dose, and neurobehavioral impairment (decreased locomotor activity) was observed in the offspring at the two highest doses. The no-effect dose (10 mg/kg/day) for pre- and postnatal developmental toxicity in rats was associated with maternal drug exposures less than that in humans at the MRHD.

Oral administration of ganaxolone (0, 20, 45, or 90 mg/kg/day) to rats on postnatal day (PND) 7 resulted in widespread apoptotic neurodegeneration in the brain (cortex, thalamus, and hippocampus) at all doses; a no-effect dose was not identified. Brain development on PND 7 in rat corresponds to that beginning in humans during the third trimester of pregnancy and continuing for the first several months to years after birth [see Use in Specific Populations (8.4)] .

8.2 Lactation

Risk Summary

Ganaxolone is excreted in human milk. Following a single oral dose of ganaxolone (300 mg), ganaxolone exposures (AUC(0-24 h)) in human milk were approximately 4 times higher than those in maternal plasma, resulting in an estimated daily dose in the infant of less than 1% of the maternal dose (see Data) . The effects of ganaxolone on milk production and the breastfed infant are unknown.

The developmental and health benefits of breastfeeding should be considered along with the mother's clinical need for ZTALMY, and any potential adverse effects on the breastfed child from ZTALMY, or from the underlying maternal condition.

Data

A study was conducted in 5 healthy adult lactating women treated with a 300 mg oral dose of ganaxolone. Ganaxolone exposures in breast milk were approximately 4 times those in maternal plasma. The calculated maximum relative infant dose for ganaxolone is approximately 0.157 mg/kg/day based on an average milk intake of 150 mL/kg/day, which is less than 1% of the maternal dose, and approximately 0.24% the labeled pediatric dose of 63 mg/kg/day.

8.4 Pediatric Use

The safety and effectiveness of ZTALMY for the treatment of seizures associated with CDD have been established in pediatric patients 2 years of age and older.

The use of ZTALMY for the treatment of seizures associated with CDD in patients 2 years of age and older is supported by a randomized, double-blind, placebo-controlled trial that included 99 pediatric patients 2 to less than 18 years of age [see Clinical Studies (14)] .

Safety and effectiveness of ZTALMY in pediatric patients below 2 years of age have not been established.

Juvenile Animal Data

Oral administration of ganaxolone (0, 20, 45, 90/150/250/500 mg/kg/day) to juvenile rats from postnatal day (PND) 7 through PND 91 resulted in deaths associated with sedation and decreased male reproductive organ weights at the mid and high doses, and delayed female sexual maturation and decreased brain weights at all doses. There were no adverse effects on neurobehavioral (locomotor activity, auditory startle response, learning and memory) or reproductive function. A no-effect dose was not established. The lowest dose producing developmental toxicity in juvenile rats (20 mg/kg/day) was associated with plasma drug exposures (AUC) less than that in pediatric patients at the maximum recommended human dose (MRHD) of 1800 mg.

Oral administration of ganaxolone (0, 10, 45, or 90 mg/kg/day) to rats on postnatal day (PND) 7 resulted in widespread neuronal death in multiple brain regions, including cortex, thalamus, and hippocampus, at all doses. The pattern and extent of neuronal death was similar to that produced by intraperitoneal injection of the positive control, the NMDA receptor antagonist MK-801 (1 mg/kg). The hippocampus, in particular, is recognized to have an important role in learning and memory. Effects of ganaxolone and MK-801 on neurobehavioral function were not assessed in this study. Brain development on PND 7 in rat corresponds to that beginning in humans during the third trimester of pregnancy and continuing for the first several months to years after birth. At the lowest-effect dose for neuronal death, plasma drug exposure in the neonatal rat was less than that in pediatric patients at the MRHD.

Oral administration of M2 (0, 15, 30, or 60 mg/kg/day), a human-specific metabolite of ganaxolone, to juvenile rats from PNDs 7 to 70 resulted in adverse effects on reproductive system development in both sexes at all doses. Effects in females included decreased corpora lutea and follicular cysts in the ovary at the high dose and signs of precocious puberty and estrous cycle disruption at all doses. Female reproductive tract changes indicative of estrous cycle disruption persisted after a 5-week recovery period at the high dose. In males, effects consisted of delayed sexual maturation and decreased epididymis and prostate weights at the high dose, seminal vesicle atrophy at mid and high doses, and decreased seminal vesicle weights at all doses. Plasma exposures (AUC) of M2 at the highest dose were 2 times those in humans at the ganaxalone MRHD of 1,800 mg, while exposures at the mid and low doses were below those in humans at the ganaxolone MRHD.

8.5 Geriatric Use

CDD is largely a disease of pediatric and young adult patients. Clinical studies of ZTALMY did not include patients 65 years of age and older.

8.6 Hepatic Impairment

Administration of ZTALMY in patients with severe hepatic impairment (Child-Pugh class C) results in elevated ganaxolone plasma concentrations [see Clinical Pharmacology (12.3)]. Therefore, dosage adjustment in these patients during titration and maintenance is required [see Dosage and Administration (2.3)] .

No dosage adjustment is necessary in patients with mild (Child-Pugh class A) or moderate (Child-Pugh class B) hepatic impairment.

9 DRUG ABUSE AND DEPENDENCE

9.1 Controlled Substance

ZTALMY contains ganaxolone, a Schedule V controlled substance (CV).

9.2 Abuse

Ganaxolone has potential for abuse. Abuse is the intentional non-therapeutic use of a drug, even once, to achieve a desired psychological or physiological effect. In a human abuse potential study, 400, 800, and 2000 mg oral doses of ZTALMY were compared to a 6 mg oral dose of lorazepam and placebo. On positive subjective measures of "drug liking", "overall drug liking", "high", "good drug effects", and "take drug again", the 400 and 800 mg doses of ZTALMY produced mean scores that were within or just outside of the acceptable placebo range and were not statistically significantly different than placebo. The 2000 mg dose of ZTALMY produced responses on these positive subjective measures that were slightly greater than the acceptable placebo range and were statistically significantly greater than placebo. Scores on these positive subjective measures for all three doses of ZTALMY were statistically significantly lower than those produced by lorazepam.

9.3 Dependence

Physical dependence is a state that develops as a result of physiological adaptation in response to repeated drug use, manifested by withdrawal signs and symptoms after abrupt discontinuation or a significant dose reduction of a drug. During clinical studies with ZTALMY, it was not possible to assess physical dependence because abrupt discontinuation of an antiepileptic medication in patients with epilepsy presents a serious safety concern. It is recommended that ZTALMY be tapered according to the dosage recommendations, unless symptoms warrant immediate discontinuation [see Dosage and Administration (2.4)and Warnings and Precautions (5.1)] .

10 OVERDOSAGE

There is limited clinical trial experience regarding overdose with ZTALMY. Unintentional overdose has been reported in 1 pediatric patient. This patient received ten times the prescribed dose. The patient was hospitalized for evaluation, including an electrocardiogram (ECG) and blood tests, and recovered.

Patients who overdose should be closely monitored and receive standard supportive care. No specific information is available regarding treatment of overdose. In the event of overdose, a certified poison control center should be contacted for updated information on the management of overdose with ZTALMY.

11 DESCRIPTION

ZTALMY (ganaxolone) oral suspension contains ganaxolone, a neuroactive steroid gamma-aminobutyric acid A (GABAA) receptor positive modulator. Ganaxolone (1-[(3R, 5S, 8R, 9S, 10S, 13S, 14S, 17S)-3-hydroxy-3, 10, 13-trimethyl-1, 2, 4, 5, 6, 7, 8, 9, 11, 12, 14, 15, 16, 17-tetradecahydrocyclopenta[a]phenanthren-17-yl]ethanone) is a methyl-substituted (at the 3β position) analog of the endogenous neurosteroid allopregnanolone, a derivative of progesterone. Its empirical formula is C22H36O2, and the molecular weight is 332.53 g/mol. The chemical structure is:

Ganaxolone is a white to off-white crystalline powder that only exists in one crystal form and has low aqueous solubility.

ZTALMY is an oral suspension of ganaxolone. Each mL of oral suspension contains 50 mg of ganaxolone. Inactive ingredients include artificial cherry flavor, citric acid, hypromellose, methylparaben, polyvinyl alcohol, propylparaben, purified water, simethicone emulsion, sodium benzoate, sodium citrate, sodium lauryl sulfate, and sucralose.

12 CLINICAL PHARMACOLOGY

12.1 Mechanism of Action

The precise mechanism by which ganaxolone exerts its therapeutic effects in the treatment of seizures associated with CDD is unknown, but its anticonvulsant effects are thought to result from positive allosteric modulation of the gamma-aminobutyric acid type A (GABAA) receptor in the CNS.

12.2 Pharmacodynamics

Cardiac Electrophysiology

At therapeutic exposures, ZTALMY does not prolong the QTc interval. QT effects of ZTALMY at high clinical exposure scenarios have not been evaluated.

12.3 Pharmacokinetics

Absorption

Following oral administration of ZTALMY, ganaxolone is absorbed with a time to maximum plasma concentration (Tmax) of 2 to 3 hours.

Effect of Food

When ZTALMY was administered with a high-fat meal, the Cmaxand AUC increased by 3- and 2-fold, respectively, when compared to administration under fasted conditions. ZTALMY was administered with food in the clinical efficacy study, Study 1 [see Dosage and Administration (2.1)] . The efficacy of ZTALMY when administered in the fasted state is unknown.

Distribution

Ganaxolone is approximately 99% protein-bound in serum.

Elimination

The terminal half-life for ganaxolone is 34 hours.

Metabolism

Ganaxolone is metabolized by CYP3A4/5, CYP2B6, CYP2C19, CYP2D6, UGT1A3, UGT1A6, UGT1A9, UGT2B7, and UGT2B15.

Excretion

Following a single oral dose of 300 mg [^14C]-ganaxolone to healthy male subjects, 55% of the total radioactivity was recovered in feces (2% as unchanged ganaxolone) and 18% of the total radioactivity dose was recovered in urine (undetected as unchanged ganaxolone).

Specific Populations

Age, sex, and race are not expected to have a clinically-relevant effect on ganaxolone pharmacokinetics, after accounting for body weight.

Pediatric Patients

After accounting for body weight, the observed pharmacokinetic exposures in patients in Study 1 [see Clinical Studies (14)] were comparable across the age groups 2 to less than 6 years of age (n=45), 6 to less than 12 years of age (n=28), and 12 to less than 18 years of age (n=16).

Patients with Renal Impairment

Following oral administration of a single 300 mg dose of ZTALMY in subjects with severe renal impairment (creatine clearance between 15 and 30 mL/min as estimated by Cockcroft-Gault formula), the AUC0-INFof ganaxolone decreased 8% and Cmaxdecreased 11% as compared to that in subjects with normal renal function (creatinine clearance ≥ 90 mL/min as estimated by Cockcroft-Gault formula). The changes in ganaxolone exposures when administered in patients with impaired renal function (creatinine clearance <90 mL/min) are not expected to be clinically significant.

Patients with Hepatic Impairment

The influence of hepatic impairment on the pharmacokinetics of ganaxolone was studied following a single oral dose of ZTALMY 300 mg. In subjects with mild hepatic impairment (Child-Pugh class A), Cmaxand AUClastincreased by 38% and 8%, respectively, compared to subjects with normal hepatic function. In subjects with moderate hepatic impairment (Child-Pugh class B), Cmaxand AUClastincreased by 45% and 50%, respectively, compared to subjects with normal hepatic function. In subjects with severe hepatic impairment (Child-Pugh class C), Cmaxand AUClastincreased by 148% and 269%, respectively, compared to subjects with normal hepatic function [see Dosage and Administration (2.3)and Use in Specific Populations (8.6)] .

Drug Interaction Studies

Clinical Studies

CYP3A4 Inducers

Coadministration of ZTALMY with rifampin, a strong inducer of CYP2C19 and CYP3A4, and a moderate inducer of CYP2B6, decreased Cmaxand AUC of ganaxolone by 57% and 68%, respectively, in healthy subjects [see Drug Interactions (7.2)] . No dedicated drug-interaction studies were conducted with moderate or weak CYP3A4 inducers.

CYP3A4 Inhibitors

Coadministration of ZTALMY with itraconazole, a strong CYP3A4 inhibitor, increased the AUC of ganaxolone by 17% in healthy subjects (Cmaxwas unchanged). Changes in ganaxolone exposures when coadministered with strong, moderate, or weak CYP3A4 inhibitors are not expected to be clinically significant.

CYP3A4 Substrates

Coadministration of ganaxolone at steady state (400 mg twice daily; 0.44 times the maximum recommended dosage) with midazolam, a sensitive CYP3A4 substrate, did not result in clinically relevant changes in exposures of the substrate in healthy subjects.

In Vitro Studies

CYP450 Enzymes

Ganaxolone does not inhibit CYP1A2, CYP2B6, CYP2C8, CYP2C9, CYP2C19, CYP2D6, or CYP3A4/5 at clinically relevant concentrations. Ganaxolone does not induce CYP1A2, CYP2B6, or CYP3A4 at clinically relevant concentrations.

UGT Enzymes

Ganaxolone is a substrate for UGT1A3, UGT1A6, UGT1A9, UGT2B7, and UGT2B15. Ganaxolone does not inhibit UGT1A1, UGT1A3, UGT1A4, UGT1A6, UGT1A9, or UGT2B7.

Transporter Systems

Ganaxolone is not a substrate of BCRP, P-gp, OCT1, OCT2, OATP1B1, or OATP1B3 at clinically relevant concentrations. Ganaxolone does not inhibit BCRP, P-gp, MATE1, MATE2-K, OAT1, OAT3, OCT1, OCT2, OATP1B1, OATP1B3, or BSEP at clinically relevant concentrations.

13 NONCLINICAL TOXICOLOGY

13.1 Carcinogenesis, Mutagenesis, Impairment of Fertility

Carcinogenesis

Oral administration of ganaxolone (150, 500, and 1000 mg/kg/day in males and 100, 300, and 1000 mg/kg/day in females) to Tg.rasH2 mice for up to 26 weeks did not result in an increase in tumors.

No carcinogenicity studies have been conducted with ganaxolone in rats.

Mutagenesis

Ganaxolone was negative for genotoxicity in in vitro (Ames and mouse lymphoma) and in vivo (rat bone marrow micronucleus) assays. The major circulating human metabolite, oxy-dehydro-ganaxolone, was negative for mutagenicity in the in vitro Ames assay but positive for clastogenicity in an in vitro mammalian chromosomal aberration test in human peripheral blood lymphocytes.

Impairment of Fertility

Oral administration of ganaxolone (0, 10, 20 or 40 mg/kg/day) to male and female rats prior to and throughout mating and continuing in females during early gestation resulted in alterations in estrous cyclicity at the high dose. There were no effects on spermatogenesis, reproductive performance and fertility, or early embryonic development. The highest dose tested (40 mg/kg/day) was associated with plasma exposures (AUC) less than that in adult humans at the maximum recommended human dose of 1800 mg.

14 CLINICAL STUDIES

The effectiveness of ZTALMY for the treatment of seizures associated with CDD in patients 2 years of age and older was established in a single, double-blind, randomized, placebo-controlled study in patients 2 to 19 years of age (Study 1, NCT03572933).

Patients enrolled in Study 1 (N=50 for ZTALMY; N=51 for placebo) had molecular confirmation of a pathogenic or likely pathogenic mutation in the CDKL5 gene, seizures inadequately controlled by at least 2 previous treatment regimens, and a minimum of 16 major motor seizures (i.e., bilateral tonic, generalized tonic-clonic, bilateral clonic, atonic, focal to bilateral tonic-clonic) per 28 days during a retrospective 2-month period prior to screening.

Patients were randomized in a 1:1 ratio to receive either ZTALMY or placebo. Following a titration period, patients in the ZTALMY arm weighing 28 kg or less received a maintenance dosage of 21 mg/kg three times daily (with a maximum daily dose of 1800 mg) while patients in the ZTALMY arm weighing more than 28 kg received a maintenance dosage of 600 mg three times daily [see Dosage and Administration (2.1)].

Ninety-six percent of patients were taking between 1 to 4 concomitant AEDs. The most frequently used concomitant AEDs (in at least 20% of patients) were valproate (34%), levetiracetam (26%), clobazam (25%), and vigabatrin (22%).

The primary efficacy endpoint was the percentage change in the 28-day frequency of major motor seizures (defined similarly as in the 2-month period prior to screening) from a 6-week prospective baseline phase during the 17-week double-blind phase. Patients treated with ZTALMY had a significantly greater reduction in the 28-day frequency of major motor seizures compared to patients receiving placebo (see Table 7).

Table 7 Change in Frequency of Major Motor Seizures per 28 days in Patients with CDD (Study 1)
Frequency of Major Motor Seizures (per 28 days) | Placebo (N=51) | ZTALMY (N=49)
Prospective Baseline Phase Median Seizure Frequency | 49 | 54
Median Percent Change from Baseline During Treatment | -7 | -31
p-value compared to placebo [Obtained from a Wilcoxon rank-sum test] |  | 0.0036

Figure 1 displays the percentage of patients by category of reduction from baseline in the 28-day frequency of major motor seizures during the 17-week double-blind phase.

Figure 1 Proportion of Patients by Category of Seizure Response for ZTALMY and Placebo in Patients with CDD (Study 1)

16 HOW SUPPLIED/STORAGE AND HANDLING

16.1 How Supplied

ZTALMY (ganaxolone) oral suspension (50 mg/mL) is a cherry flavored white to off-white suspension supplied in a 4 fl. oz (135 mL) round natural high density polyethylene (HDPE) bottle with a propylene child-resistant cap containing 110 mL of ZTALMY oral suspension.

ZTALMY is packaged in a carton with 1 bottle (NDC 81583-100-01).

16.2 Storage and Handling

Store ZTALMY in its original bottle in an upright position at 20°C to 25°C (68°F to 77°F); excursions permitted from 15°C to 30°C (59°F to 86°F) [see USP Controlled Room Temperature]. Keep the cap tightly closed. Use within 30 days of first opening the bottle, then discard any remainder.

17 PATIENT COUNSELING INFORMATION

Advise the patient to read the FDA-approved patient labeling (Medication Guide and Instructions for Use).

Somnolence and Sedation

Caution patients about operating hazardous machinery, including motor vehicles, until they are reasonably certain that ZTALMY does not affect them adversely (e.g., impair judgment, thinking, or motor skills) [see Warnings and Precautions (5.1)] .

Suicidal Thinking and Behavior

Counsel patients, their caregivers, and their families that antiepileptic drugs, including ZTALMY, may increase the risk of suicidal thoughts and behavior and advise them to be alert for the emergence or worsening of symptoms of depression, any unusual changes in mood or behavior, or the emergence of suicidal thoughts, behavior, or thoughts of self-harm. Instruct patients, caregivers, and families to report behaviors of concern immediately to healthcare providers [see Warnings and Precautions (5.2)] .

Withdrawal of Antiepileptic Drugs (AEDs)

Advise patients not to discontinue use of ZTALMY without consulting with their healthcare provider. ZTALMY should normally be gradually withdrawn to reduce the potential for increased seizure frequency and status epilepticus [see Dosage and Administration (2.4)and Warnings and Precautions (5.3)] .

Administration information

Advise patients who are prescribed ZTALMY to use the adapter and oral dosing syringes provided by their pharmacist [see Dosage and Administration (2.2)and Instructions for Use] .

Instruct patients to take ZTALMY with food [see Dosage and Administration (2.1)] .

Instruct patients to shake ZTALMY thoroughly for at least 1 minute and then wait for 1 minute before measuring and administering each dose [see Dosage and Administration (2.2)and Instructions for Use] .

Instruct patients to discard any unused ZTALMY oral suspension after 30 days of first opening the bottle [see Dosage and Administration (2.2)and How Supplied/Storage and Handling (16.2)] .

Pregnancy Registry

Advise patients to notify their healthcare provider if they become pregnant or intend to become pregnant during ZTALMY therapy. Encourage women who are taking ZTALMY to enroll in the North American Antiepileptic Drug (NAAED) Pregnancy Registry if they become pregnant. This registry is collecting information about the safety of antiepileptic drugs during pregnancy [see Use in Specific Populations (8.1)] .

Potential for Abuse

Advise patients that ZTALMY can be abused or lead to dependence [see Drug Abuse and Dependence (9)] .

Manufactured for:
Immedica Pharma AB, Stockholm, Sweden

Marketed by:
Immedica Pharma US Inc., Chicago, IL 60642
© Immedica Pharma US Inc. All rights reserved.
ZTALMY is a registered trademark of Immedica Pharma US Inc.

MEDICATION GUIDE
ZTALMY®(zuh tal' mee)
(ganaxolone)
oral suspension, CV

What is the most important information I should know about ZTALMY?
ZTALMY can cause serious side effects, including:

- ZTALMY may cause sleepiness. Taking ZTALMY with central nervous system (CNS) depressants including alcohol may increase sleepiness. Do notdrive, operate heavy machinery, or do other dangerous activities until you know how ZTALMY affects you or your child.
- Like other antiepileptic drugs, ZTALMY may cause suicidal thoughts or actions in a very small number of people, about 1 in 500.
  Call a healthcare provider right away if you or your child have any of these symptoms, especially if they are new, worse, or worry you:

- thoughts about suicide or dying
- attempt to commit suicide
- new or worse depression
- new or worse anxiety
- feeling agitated or restless
- panic attacks

- trouble sleeping (insomnia)
- new or worse irritability
- acting aggressive, being angry, or violent
- acting on dangerous impulses
- an extreme increase in activity and talking (mania)
- other unusual changes in behavior or mood

How can I watch for early symptoms of suicidal thoughts and actions?

- Pay attention to any changes, especially sudden changes in mood, behaviors, thoughts, or feelings.
- Keep all follow-up visits with your healthcare provider as scheduled.

- Do not stop taking ZTALMY without first talking to your healthcare provider. Stopping a seizure medicine such as ZTALMY suddenly can cause you or your child to have seizures more often or seizures that do not stop (status epilepticus).

Call your healthcare provider between visits as needed, especially if you are worried about symptoms.

WHAT IS ZTALMY?

- ZTALMY is a prescription medicine that is used to treat seizures associated with cyclin-dependent kinase-like 5 (CDKL5) deficiency disorder (CDD) in people 2 years of age and older.
- ZTALMY is a federally controlled substance (CV) because it contains ganaxolone that can be abused and lead to dependence. Keep ZTALMY in a safe place to prevent misuse and abuse. Selling or giving away ZTALMY may harm others and is against the law. Tell your healthcare provider if you or your child have ever abused or been dependent on alcohol, prescription medicines, or street drugs.
- It is not known if ZTALMY is safe and effective in children under 2 years of age.

Before taking ZTALMY, tell your healthcare provider about all of your or your child's medical conditions, including if you or your child:

- drink alcohol.
- have or have had depression, mood problems, or suicidal thoughts or behavior.
- have abused or been dependent on prescription medicines, street drugs, or alcohol.
- have liver problems.
- are pregnant or plan to become pregnant. Tell your healthcare provider right away if you or your child become pregnant while taking ZTALMY. You and your healthcare provider will decide if you or your child should take ZTALMY while pregnant.
  - if you or your child become pregnant while taking ZTALMY, talk to your healthcare provider about registering with the North American Antiepileptic Drug Pregnancy Registry. You can enroll in this registry by calling 1-888-233-2334 or go to http://www.aedpregnancyregistry.org/. The purpose of this registry is to collect information about the safety of antiepileptic drugs during pregnancy.
- are breastfeeding or plan to breastfeed. ZTALMY may pass into breast milk. Talk to your healthcare provider about the best way to feed your or your child's baby while taking ZTALMY.

Tell your healthcare provider about all the medicines you or your child take,including prescription and over-the-counter medicines, vitamins, and herbal supplements. ZTALMY may affect the way other medicines work, and other medicines may affect how ZTALMY works. Do not stop or start taking other medicines without talking to your healthcare provider.
Especially tell your healthcare provider if you or your child take:

- alcohol
- opioids
- antidepressants

Know the medicines you or your child take. Keep a list of them to show your healthcare provider or pharmacist when you or your child get a new medicine.

How should I take ZTALMY?

- Read the Instructions for Useat the end of this Medication Guide for information on the right way to use ZTALMY.
- Take or give ZTALMY exactly as your healthcare provider tells you.
- Your healthcare provider will tell you how much ZTALMY to take or give and when to take or give it.
- Measure each dose of ZTALMY using the bottle adapter and oral dosing syringes provided by your pharmacist. Do not use a household teaspoon or tablespoon. If your dose of ZTALMY is less than 1 mL, your pharmacist will provide you with an appropriately sized syringe to take or give ZTALMY.
- Take or give ZTALMY with food.
- In case of overdose, get medical help or contact a live Poison Center expert right away.

What should I avoid while taking ZTALMY?

- Do notdrive, operate heavy machinery, or do other dangerous activities until you know how ZTALMY affects you or your child. ZTALMY may cause you or your child to feel sleepy.

What are the possible side effects of ZTALMY?
ZTALMY can cause serious side effects, including:

- See " What is the most important information I should know about ZTALMY?"

The most common side effects of ZTALMY include:

- sleepiness
- fever
- excessive saliva or drooling
- seasonal allergy

These are not all of the possible side effects of ZTALMY. For more information ask your healthcare provider or pharmacist.
Tell your healthcare provider about any side effect that bothers you or your child, or that does not go away.
Call your doctor for medical advice about side effects. You may report side effects to FDA at 1-800-FDA-1088.
You may also contact Immedica Pharma US at 1-844-627-4687.

How should I store ZTALMY?

- Store ZTALMY at 68°F to 77°F (20°C to 25°C).
- Always store ZTALMY in its original bottle in an upright position.
- Keep the child-resistant cap tightly closed.
- Use ZTALMY within 30 days of first opening the bottle. Throw away (dispose of) any unused medicine after 30 days.

Keep ZTALMY and all medicines out of the reach of children.

General Information about the safe and effective use of ZTALMY.
Medicines are sometimes prescribed for purposes other than those listed in a Medication Guide. Do not use ZTALMY for a condition for which it was not prescribed. Do not give ZTALMY to other people, even if they have the same symptoms that you have. It may harm them.
You can ask your pharmacist or healthcare provider for information about ZTALMY that is written for health professionals.

What are the ingredients in ZTALMY?
Active ingredient: ganaxolone
Inactive ingredients:artificial cherry flavor, citric acid, hypromellose, methylparaben, polyvinyl alcohol, propylparaben, purified water, simethicone emulsion, sodium benzoate, sodium citrate, sodium lauryl sulfate and sucralose.
Manufactured for Immedica Pharma AB, Stockholm, Sweden
Marketed by Immedica Pharma US Inc., Chicago, IL 60642
For more information, go to www. ZTALMY.com or call 844-IMMEDICA (1-844-627-4687).
© Immedica Pharma US Inc. All rights reserved.
ZTALMY is a registered trademark of Immedica Pharma US Inc.

This Medication Guide has been approved by the U.S. Food and Drug Administration

Issued: Issued: 11/2025

INSTRUCTIONS FOR USE

ZTALMY®(zuh-tal' mee)
(ganaxolone)
oral suspension, CV
50 mg/mL

Be sure that you read, understand, and follow these instructions carefully to ensure proper dosing of the oral suspension.

Important:

- Follow your healthcare provider's instructions for how to take or give ZTALMY.
- ZTALMY should always be given with food.
- Ask your healthcare provider or pharmacist if you are not sure how to prepare, take, or give the prescribed dose of ZTALMY.
- Always use the oral syringe provided by your pharmacist to make sure you measure the right amount of ZTALMY.
- Do not use ZTALMY after the expiration date on the package and each bottle.
- Use ZTALMY within 30 days of first opening the bottle.
- After 30 days of first opening the bottle, safely throw away (dispose of) any ZTALMY that has not been used.

Each package contains:

1bottle of ZTALMY with a child resistant cap:

Supplies not includedin the package:

- press-in bottle adapter
- oral syringe

You can get a press-in bottle adapter and oral syringes from your pharmacy. Your pharmacist can help you choose the right press-in bottle adapter and oral syringe to use with ZTALMY.

Call your pharmacist right away if you do not have a press-in bottle adapter and the right sized oral syringe to use with your medicine.

Note:If you lose or damage an oral syringe, or cannot read the markings, contact your pharmacist for a new oral syringe.

Follow the instructions below to use the press-in bottle adapter and oral syringe to measure and take or give ZTALMY.

Prepare the bottle

- Hold the bottle in your hand and shake it up and down well for 1 minute.
  Always shake the bottle well for 1 minute then let the bottle stand for 1 minute so that any foam build up during shaking can settle before measuring and giving each doseof ZTALMY. This helps you measure the correct amount of medicine.
  Note:This step is for each dose of the medicine.

- Remove the child-resistant cap by pushing down while turning the cap to the left (counter-clockwise).

- Puncture and peel off the induction seal from the bottle.
  Note:This step is only for the first use of the bottle.

- Push the press-in-bottle adapter firmly into the bottle. Firmly grasp the bottle in one hand and insert the press-in bottle adapter all the way in the bottle with the other hand using constant pressure. Make sure the press-in bottle adaptor is fully inserted. If not fully inserted, small parts such as the press-in bottle adaptor may become a choking hazard for children and pets.
  Note: Do notremove the press-in bottle adapter from the bottle after it is inserted.

Prepare the dose

Your healthcare provider will tell you how much ZTALMY to take or give.

- Gather the oral syringe, push the plunger all the way down then insert the tip of the oral syringe fully into the press-in bottle adapter. With the oral syringe in place, turn the bottle upside down.

- Slowly pull the plunger of the oral syringe to withdraw the dose of ZTALMY needed. Line up the end of the plunger with the marking for your dose of ZTALMY.
  What to do if you see air bubbles:
  If there are air bubbles in the oral syringe, keep the bottle upside down and slowly push the plunger so that all of the liquid flows back into the bottle.
  Repeat step 6 until air bubbles are gone.

- When you have measured the correct amount of ZTALMY, leave the oral syringe in the press-in bottle adapter and turn the bottle right side up.

- Carefully remove the oral syringe from the press-in bottle adapter.

Take or give ZTALMY

- Place the tip of the oral syringe against the inside of the cheek and gently push the plunger until all of the ZTALMY in the oral syringe is taken or given.
  Do notforcefully push the plunger.
  Do notdirect the medicine to the back of the mouth or throat. This may cause choking.

- Screw the child-resistant cap back on the bottle tightly by turning the cap to the right (clockwise). Do not remove the press-in bottle adapter. The child-resistant cap will fit over it.

How should I store ZTALMY?

- Store ZTALMY at 68°F to 77°F (20°C to 25°C).
- Always store ZTALMY in its original bottle in an upright position.
- Keep the child-resistant cap tightly closed.
- Use within 30 days of first opening the bottle. Throw away (dispose of) any unused medicine after 30 days.

Keep ZTALMY and all medicines out of the reach of children.

Helpline Details

For additional assistance, call the toll-free helpline at 844-IMMEDICA (1-844-627-4687). Hours: Monday - Friday 8:00 am to 6:00 pm EST

Frequently asked Questions:

Q: | What if there are air bubbles in the oral syringe?
A: | Slowly push the liquid back into the bottle and repeat step 6 until the air bubbles are gone.

Manufactured for Immedica Pharma AB, Stockholm, Sweden
Marketed by Immedica Pharma US Inc., Chicago, IL 60642
For more information, go to www.ZTALMY.com or call 1-484-801-4670.
© Immedica Pharma US Inc. All rights reserved.
ZTALMY is a registered trademark of Immedica Pharma US Inc.

Issued: 11/2025

PRINCIPAL DISPLAY PANEL - 50 mg/mL Bottle Label

NDC 81583-100-01
Rx Only

Ztalmy®
(ganaxolone)
oral suspension
50 mg/mL

CV

For Oral Administration Only

Recommended Dosage:
See prescribing information.
Administer with the provided
syringe.

Date of first opening
_____/_____/_____.
Discard unused portion
30 days after first opening.

PRINCIPAL DISPLAY PANEL - 50 mg/mL Bottle Carton

Rx Only

NDC 81583-100-01

Ztalmy®
(ganaxolone) oral suspension

50 mg/mL

CV

For Oral Administration Only

Read enclosed instructions before using
this product.
Pharmacist: Dispense the enclosed
Medication guide to each patient.

110 mL